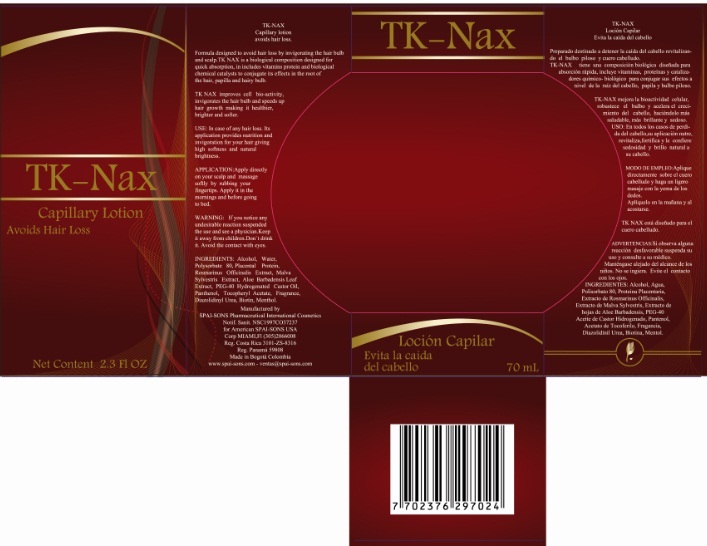 DRUG LABEL: TK-NAX
NDC: 66854-020 | Form: LIQUID
Manufacturer: SPAI-SONS PHARMACEUTICAL INTERNATIONAL COSMETICS
Category: otc | Type: HUMAN OTC DRUG LABEL
Date: 20120607

ACTIVE INGREDIENTS: BIOTIN 0.01 mL/100 mL
INACTIVE INGREDIENTS: ALCOHOL; WATER; POLYOXYL 40 HYDROGENATED CASTOR OIL; POLYSORBATE 80; HYDROLYZED PLACENTAL PROTEIN (BOVINE); ROSMARINUS OFFICINALIS FLOWERING TOP; MALVA SYLVESTRIS FLOWERING TOP; PANTHENOL; .ALPHA.-TOCOPHEROL ACETATE, D-; DIAZOLIDINYL UREA; MENTHOL; ALOE VERA LEAF

TK-NAX

ACTIVE INGREDIENT

Biotin is a major component of the formulation acts to strengthen the hair follicle and prevents hair loss as well. It is nutrient for the hair root and helps oxygenate the hair turn slowing the loss. Provides resilience and resistence to hair.

PURPOSE

1. Delays the aging process of the capillary follicle and accelerates its growth

2. Repairs and protects the structure of the follicle, prolonging hair life.

This product must be keep out of children

INDICATIONS AND USAGE

This product is for topical application directly on the hair follicle

WARNINGS

Avoid contact with eyes, if they do wash with water. If swallowed contact a physician immediately

DOSAGE AND ADMINISTRATION

Apply every 12 hours on scapl and activate tapping softly with fingertips

INACTIVE INGREDIENT

This is a liquid product prepared with the technology needed to provide the hair follicle absorption of the active ingredients, plus inactive ingredients contribute to the regeneration of the hair fiber by providing a strengthening therefore.

IMAGE OF THE CARTON LABEL